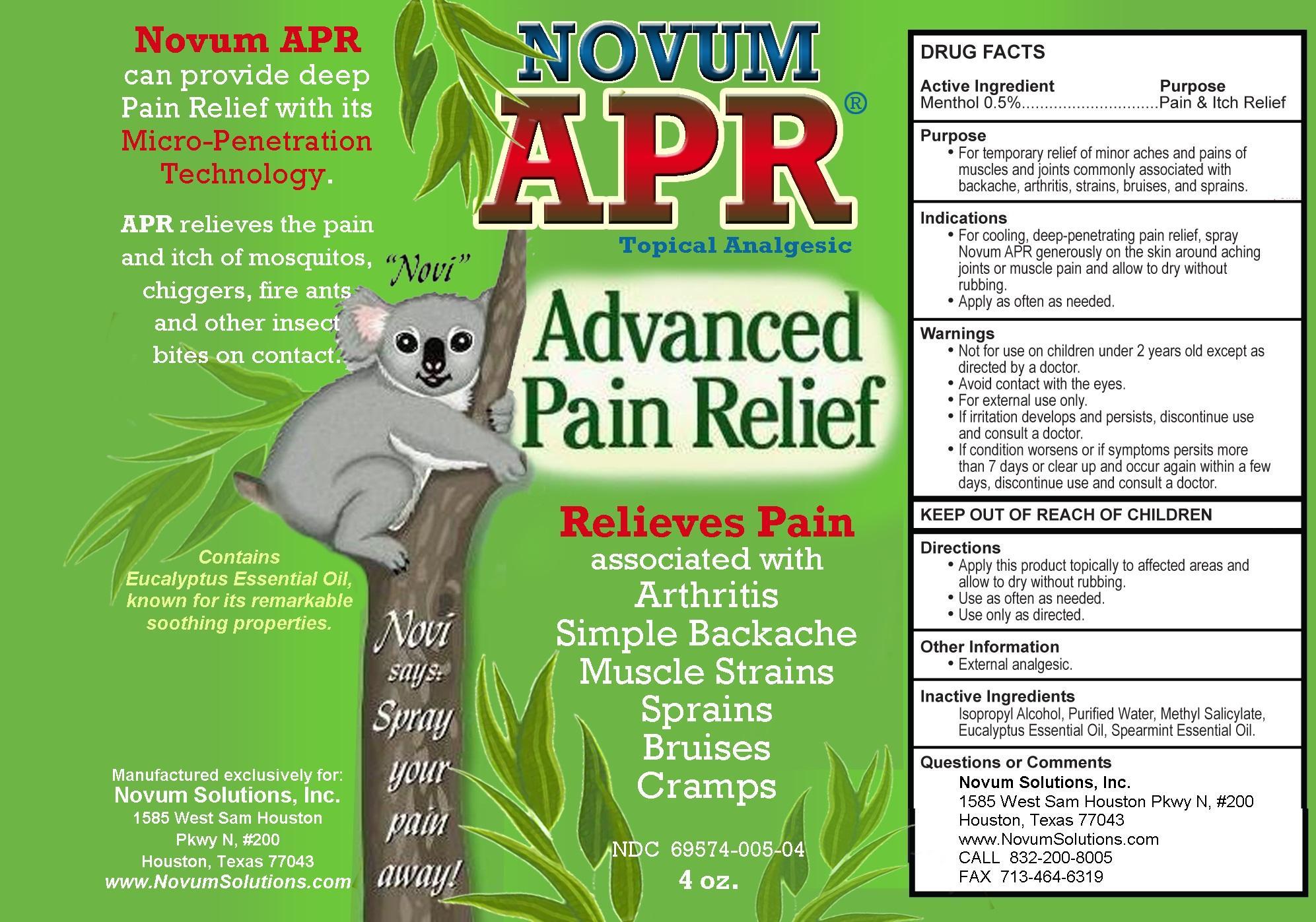 DRUG LABEL: NOVUM
NDC: 69574-005 | Form: SPRAY
Manufacturer: NOVUM SOLUTIONS INC
Category: otc | Type: HUMAN OTC DRUG LABEL
Date: 20250407

ACTIVE INGREDIENTS: MENTHOL 0.5 g/100 mL
INACTIVE INGREDIENTS: ISOPROPYL ALCOHOL; METHYL SALICYLATE; EUCALYPTUS OIL; SPEARMINT OIL; WATER

Drug Facts

Topical Burn Cream Plus Pain Relief

Active Ingredient

Menthol 0.5%

Purpose

Pain & Itch Relief

For the temporary relief of minor aches and pains of muscles and joints commonly associated with backache, arthritis, strains, bruises, and sprains.

Indications

For cooling, deep-penetrating pain relief, spray Novum APR generously on the skin around aching joints or muscle pain and allow to dry without rubbing.
Apply as often as needed.

Warnings

Not intended for use on children under 2 years old except as directed by a doctor.
Avoid contact with eyes.
For external use only.
If irritation develops and persists, discontinue use and consult a doctor.
If condition worsens or if symptoms persist more than 7 days or clear up and occur again within a few days, discontinue use and consult a doctor.

KEEP OUT OF REACH OF CHILDREN KEEP OUT OF REACH OF CHILDREN

KEEP OUT OF REACH OF CHILDREN

Directions

Apply this product topically to affected areas and allow to dry without rubbing.
Use as often as needed.
Use only as directed.

Other Information

External analgesic

Inactive Ingredients

ISOPROPYL ALCOHOL, PURIFIED WATER, METHYL SALICYLATE, EUCALYPTUS ESSENTIAL OIL, SPEARMINT ESSENTIAL OIL.

Questions or Comments

Novum Solutions, Inc.

1585 West Sam Houston Pkwy N, #820

Houston, TX 77403

www.NovumSolutions.com

CALL 832-200-8005

FAX 713-464-6319